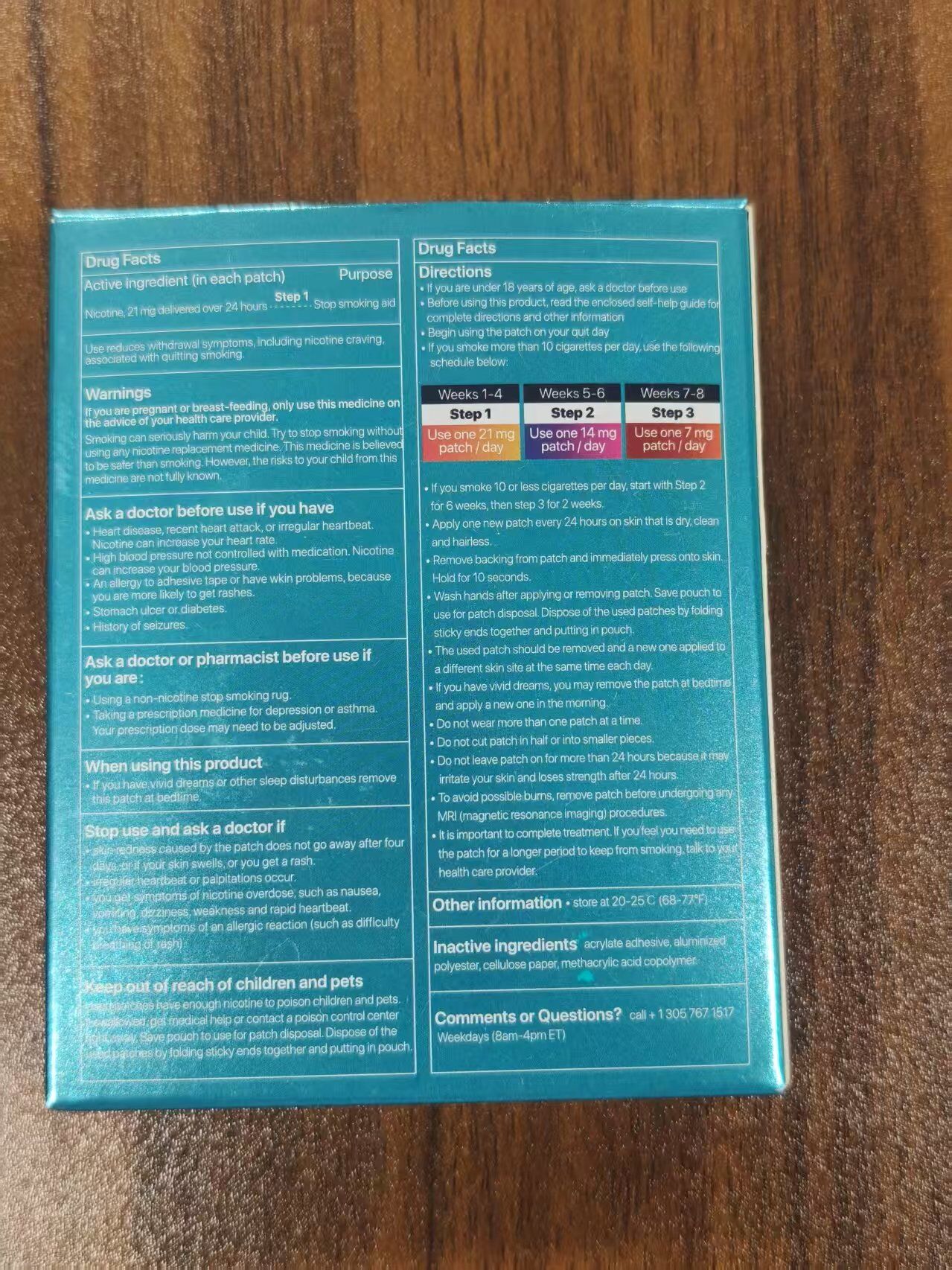 DRUG LABEL: SEFUDUN QUIT SMOKING NICOTINE PATCHES
NDC: 83804-001 | Form: PATCH
Manufacturer: Shenzhen Shandian Jingling Technology Co., Ltd.
Category: otc | Type: HUMAN OTC DRUG LABEL
Date: 20250327

ACTIVE INGREDIENTS: NICOTINE 21 mg/1 1
INACTIVE INGREDIENTS: POLYESTER-5 (TG-38); ACRYLIC ACID; METHACRYLIC ACID - METHYL METHACRYLATE COPOLYMER (1:1)

SEFUDUN QUIT SMOKING NICOTINE PATCHES

ACTIVE INGREDIENT

nicotine

PURPOSE

nicotine patch

KEEP OUT OF REACH OF CHILDREN SECTION

WARNINGS

For external use only

DOSAGE AND ADMINISTRATION

1. Clean your arms thoroughly
2. Take out the patch and stick it on your arm
3. Valid for up to 24 hours

INACTIVE INGREDIENT

methacrylic acid copolymer
POLYESTER-5 (TG-38)
ACRYLIC ACID

INDICATIONS AND USAGE

Use reduces withdrawal symptoms, ineluding nicotine cravingassocated with qultting sroking